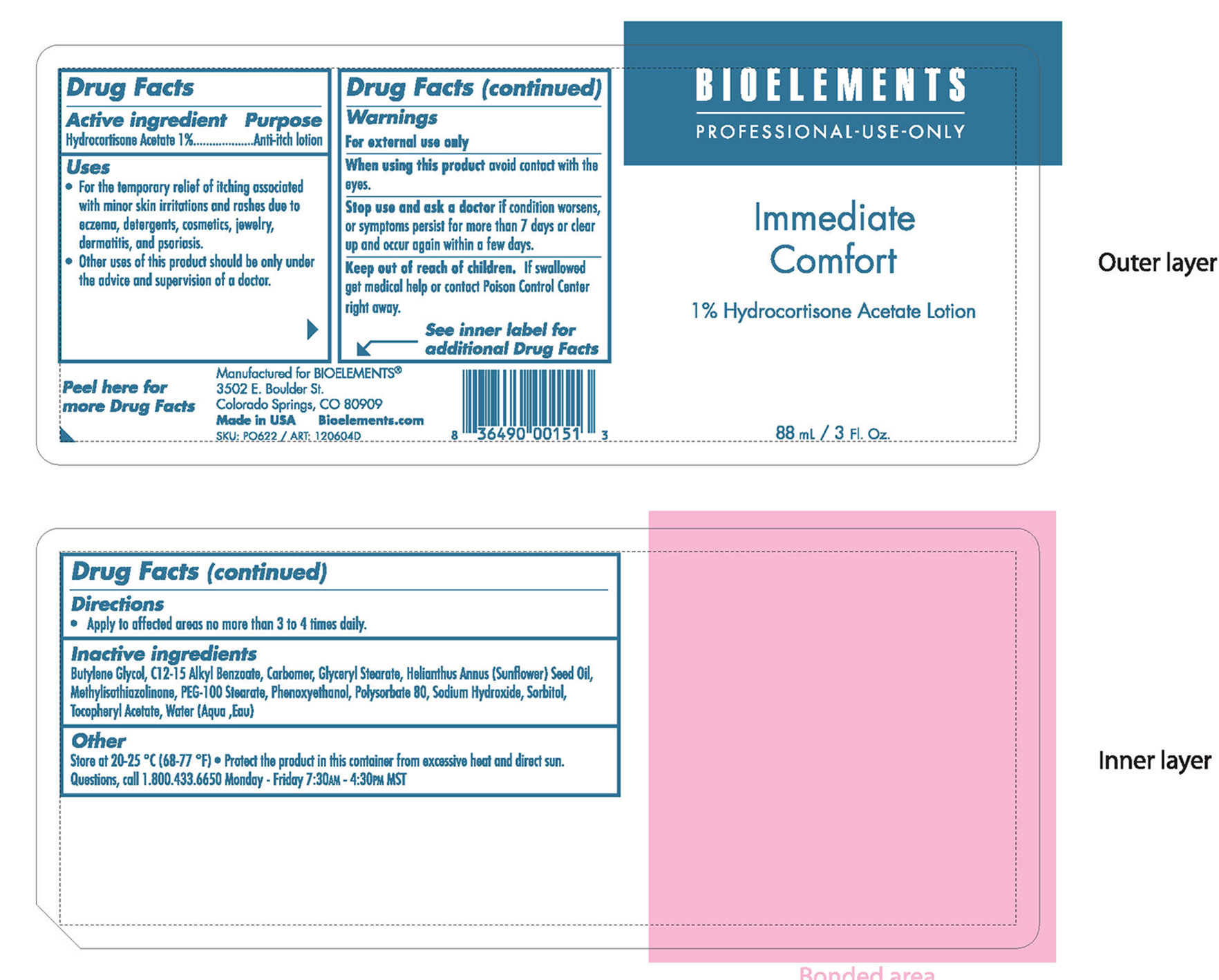 DRUG LABEL: 
                           
NDC: 49825-126 | Form: LOTION
Manufacturer: Bioelements, Inc.
Category: prescription | Type: HUMAN PRESCRIPTION DRUG LABEL
Date: 20120824

ACTIVE INGREDIENTS: HYDROCORTISONE ACETATE 0.088 mL/88 mL
INACTIVE INGREDIENTS: BUTYLENE GLYCOL; ALKYL (C12-15) BENZOATE; CARBOMER HOMOPOLYMER TYPE C (ALLYL PENTAERYTHRITOL CROSSLINKED); GLYCERYL MONOSTEARATE; SUNFLOWER OIL; METHYLISOTHIAZOLINONE; PEG-100 STEARATE; PHENOXYETHANOL; POLYSORBATE 80; SODIUM HYDROXIDE; SORBITOL; .ALPHA.-TOCOPHEROL ACETATE; WATER

Immediate Comfort

Active Ingredient Purpose

Hydrocortisone Acetate 1% Anti-itch lotion

Uses

For the temporary relief of itching associated with minor skin irritations and rashes due to exzema, detergents, cosmetics, jewelry, dermatitis, psoriasis.

Other uses of this product should be only under the advice and supervision of a doctor.

Keep out of reach of children. If swallowed get medical help or contact a poison control center right away.

Stop use and ask a doctor if condition worsens or symptoms persist for more than 7 days or clear up and occur again within a few days.

Warnings

For external use only

When using this product avoid contact with the eyes.

Directions

Apply to affected area no more than 3 to 4 times daily.

Inactive ingredients

Butylene Glycol, C12-15 Alkyl Benzoate, Carbomer, Glyceryl Stearate, Helianthuus annus (sunflower) Seed Oil, Methylisothiazolinone, PEG-100 Stearate, Phenoxyethanol, Ploysorbate 80, Sodium Hydroxide, Sorbitol, Tocopheryl Acetate, Water (Aqua, Eau)

PACKAGE LABEL

Bioelements PROFESSIONAL-USE-ONLY

Immediate comfort

1% Hydrocortisone Acetate Lotion

88 ml/ 3 Fl Oz.